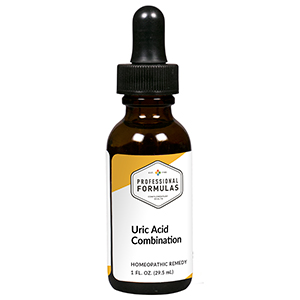 DRUG LABEL: Uric Acid Combination
NDC: 63083-9307 | Form: LIQUID
Manufacturer: Professional Complementary Health Formulas
Category: homeopathic | Type: HUMAN OTC DRUG LABEL
Date: 20190815

ACTIVE INGREDIENTS: SODIUM CARBONATE 3 [hp_X]/29.5 mL; COLCHICUM AUTUMNALE BULB 4 [hp_X]/29.5 mL; STRYCHNOS NUX-VOMICA SEED 6 [hp_X]/29.5 mL; TOXICODENDRON PUBESCENS LEAF 6 [hp_X]/29.5 mL; FERROSOFERRIC PHOSPHATE 8 [hp_X]/29.5 mL; LITHIUM CARBONATE 8 [hp_X]/29.5 mL; GLUTAMINE 12 [hp_X]/29.5 mL; 1,3-BIS(BENZOTHIAZOL-2-YLTHIOMETHYL)UREA 12 [hp_X]/29.5 mL; URIC ACID 12 [hp_X]/29.5 mL
INACTIVE INGREDIENTS: ALCOHOL; WATER

R307

ACTIVE INGREDIENTS

Natrum carbonicum 3X
Colchicum autumnale 4X
Nux vomica 6X
Rhus toxicodendron 6X
Ferrum phosphoricum 8X
Lithium carbonicum 8X
Glutamine 12X
Urea 12X
Uricum acidum 12X

QUESTIONS

Professional Formulas

PO Box 2034 Lake Oswego, OR 97035

INDICATIONS

For the temporary relief of minor joint pain or swelling, occasional headache, runny nose, skin irritation, or nausea.*

PURPOSE

*Claims based on traditional homeopathic practice, not accepted medical evidence. Not FDA evaluated.

WARNINGS

Consult a doctor if condition worsens or if symptoms persist. Keep out of the reach of children. In case of overdose, get medical help or contact a poison control center right away. If pregnant or breastfeeding, ask a healthcare professional before use.

Keep out of the reach of children.

PREGNANCY OR BREAST FEEDING

If pregnant or breastfeeding, ask a healthcare professional before use.

DIRECTIONS

Place drops under tongue 30 minutes before/after meals. Adults and children 12 years and over: Take 10 drops up to 3 times per day. Consult a physician for use in children under 12 years of age.

OTHER INFORMATION

Tamper resistant. If seal is broken, do not use. After opening, close container tightly and store at room temperature away from heat.

INACTIVE INGREDIENTS

40% ethanol, purified water.

LABEL

Est 1985

Professional Formulas

Complementary Health

Uric Acid Combination

Homeopathic Remedy

1 FL. OZ. (29.5 mL)